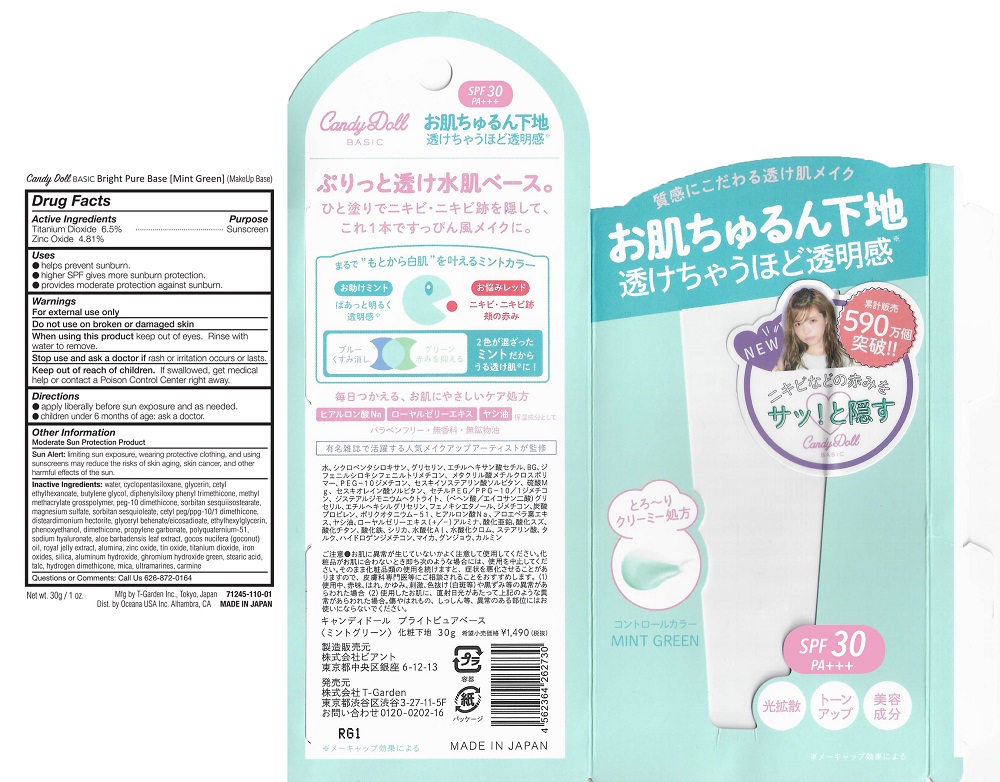 DRUG LABEL: Candy Doll Basic Bright Pure Base Mint Green
NDC: 71245-110 | Form: LOTION
Manufacturer: T-Garden Inc
Category: otc | Type: HUMAN OTC DRUG LABEL
Date: 20170918

ACTIVE INGREDIENTS: ZINC OXIDE 1.59 g/30 g; TITANIUM DIOXIDE 1.86 g/30 g
INACTIVE INGREDIENTS: WATER; GLYCERIN; BROWN IRON OXIDE

Candy Doll Basic Bright Pure Base Mint Green

Active Ingredients

Titanium Dioxide 6.5%

Zinc Oxide 4.81%

Purpose

Sunscreen

Warnings

For external use only

Do not use on broken or damaged skin

When Using

When using this product keep out of eyes. Rinse with water to remove.

Stop use and ask a doctor if rash or irritation occurs or lasts.

Keep Out of Reach of Children

Directions

apply liberally before sun exposure and as needed

children under 6 months of age: ask a doctor

Inactive Ingredients

water, cyclopentasiloxane, glycerin, cetyl ethylhexanoate, butylene glycol, diphenylsiloxy phenyl tremethicone, methyl methacrylate crosspolymer, PEG-10 dimethicone, sorbitan sesquiisostearate, magnesium sulfate, sorbitan sesquioleate, cetyl PEG/PPG-10/1 dimethicone, disteardimonium hectorite, aluminum hydroxide, glyceryl behenate/eicosadioate, stearic acid, talc, ethylhexylglycerin, phenoxyethanol, dimethicone, propylene carbonate, hydrogen dimethicone, polyquaternium-51, sodium hyaluronate, aloe barbadensis leaf extract, cocos nucifera (coconut) oil, royal jelly extract, alumina, iron oxides, silica, aluminum hydroxide, chromium hydroxide green, stearic acid, talc, hydrogen dimethicone, mica, ultramarines, carmine, tin oxide,

Questions

Questions or Comments: Call Us 626-872-0164

PDP Image

CandyDoll Basic Bright Pure Base Mint Green.jpg